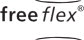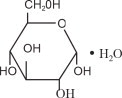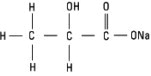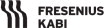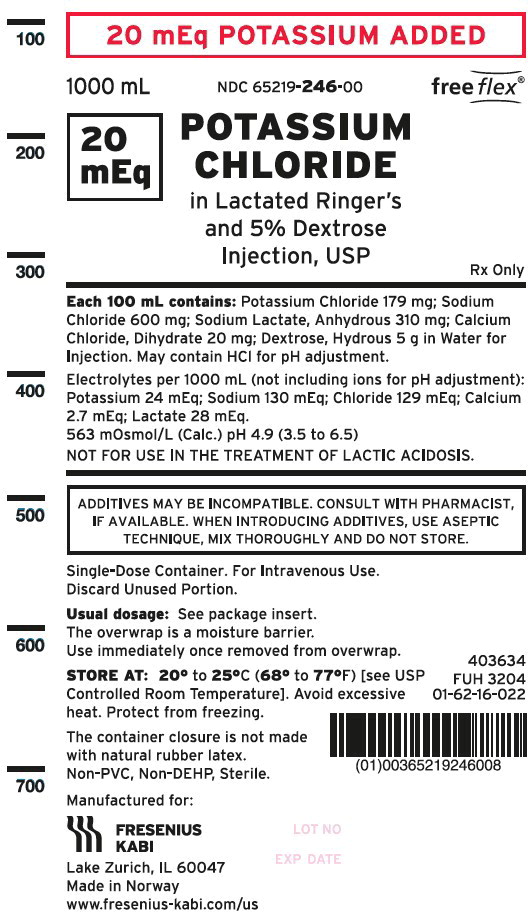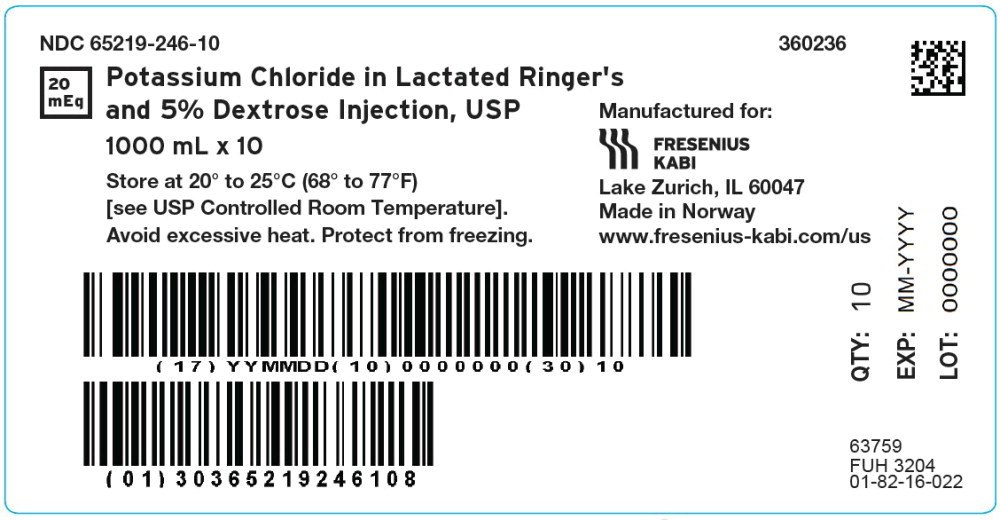 DRUG LABEL: Potassium Chloride in Lactated Ringers and Dextrose

NDC: 65219-246 | Form: INJECTION, SOLUTION
Manufacturer: Fresenius Kabi USA, LLC
Category: prescription | Type: HUMAN PRESCRIPTION DRUG LABEL
Date: 20240522

ACTIVE INGREDIENTS: POTASSIUM CHLORIDE
 1.79 g/1000 mL; SODIUM CHLORIDE
 6 g/1000 mL; CALCIUM CHLORIDE
 0.2 g/1000 mL; SODIUM LACTATE
 3.1 g/1000 mL; DEXTROSE MONOHYDRATE
 50 g/1000 mL
INACTIVE INGREDIENTS: WATER

INTRAVENOUS SOLUTIONS WITH POTASSIUM CHLORIDE POTASSIUM CHLORIDE IN LACTATED RINGER'S AND 5% DEXTROSE INJECTION, USP

Flexible Plastic Container
Rx only

DESCRIPTION

Intravenous solution with potassium chloride (I.V. solutions with KCl) is a sterile and nonpyrogenic solution in water for injection. This solution is for administration by intravenous infusion only.

See Table 1 below for summary of content and characteristics of this solution.

Table 1 |  | COMPOSITION (g/L) |  |  |  |  | Calculated Osmolarity (mOsmol/L)
Potassium Chloride in Lactated Ringer's and 5% Dextrose Injection, USP |  | COMPOSITION (g/L) |  |  |  |  | Calculated Osmolarity (mOsmol/L)
mEq Potassium Added | Size (mL) | Dextrose, Hydrous | Potassium Chloride | Sodium Chloride | Sodium Lactate, Anhydrous | Calcium Chloride Dihydrate | Calculated Osmolarity (mOsmol/L)
20 mEq | 1000 | 50 | 1.79 | 6 | 3.1 | 0.2 | 563

pH | Approx. Ionic Concentrations (mEq/L) |  |  |  |  | Approx. kcal/L
pH | Calcium (Ca++) | Sodium (Na+) | Potassium (K+) | Chloride (Cl-) | Lactate | Approx. kcal/L
4.9 (3.5 to 6.5) | 2.7 | 130 | 24 | 129 | 28 | 179

May contain HCl for pH adjustment.

The solution contains no bacteriostat, antimicrobial agent or added buffer and each is intended only for use as a single-dose injection. When smaller doses are required the unused portion should be discarded.

This solution is a parenteral fluid, nutrient and/or electrolyte replenisher.

Dextrose, USP is chemically designated D-glucose, monohydrate (C6H12O6 • H2O), a hexose sugar freely soluble in water. It has the following structural formula:

Potassium Chloride, USP is chemically designated KCl, a white granular powder freely soluble in water. Sodium Chloride, USP is chemically designated NaCl, a white crystalline powder freely soluble in water.

Calcium Chloride, USP is chemically designated calcium chloride dihydrate (CaCl2 • 2H2O), white fragments or granules freely soluble in water.

Sodium Lactate, USP is chemically designated monosodium lactate [CH3CH(OH)COONa], a 50% aqueous solution miscible in water. It has the following structural formula:

Water for Injection, USP is chemically designated H20.

The flexible plastic container is fabricated from a specially formulated non-plasticized, film containing polypropylene and thermoplastic elastomers (freeflex® bag). Water can permeate from inside the container into the overwrap but not in amounts sufficient to affect the solution significantly. Solutions in contact with the plastic container may leach out certain chemical components from the plastic in very small amounts; however, biological testing was supportive of the safety of the plastic container materials. Exposure to temperatures above 25°C/77°F during transport and storage will lead to minor losses in the moisture content. Higher temperatures lead to greater losses. It is unlikely that these minor losses will lead to clinically significant changes within the expiration period.

CLINICAL PHARMACOLOGY

When administered intravenously, this solution provides a source of water and electrolytes with carbohydrate calories.

Solutions containing carbohydrate in the form of dextrose restore blood glucose levels and provide calories. Carbohydrate in the form of dextrose may aid in minimizing liver glycogen depletion and exerts a protein- sparing action. Dextrose injected parenterally undergoes oxidation to carbon dioxide and water.

Calcium chloride in water dissociates to provide calcium (Ca^++) and chloride (Cl^-) ions. They are normal constituents of the body fluids and are dependent on various physiologic mechanisms for maintenance of balance between intake and output. Approximately 80% of body calcium is excreted in the feces as insoluble salts; urinary excretion accounts for the remaining 20%.

Sodium lactate provides sodium (Na^+) and lactate (C3H5O^-) ions. The lactate anion is in equilibrium with pyruvate and has an alkalizing effect resulting from simultaneous removal by the liver of lactate and hydrogen ions. In the liver, lactate is metabolized to glycogen which is ultimately converted to carbon dioxide and water by oxidative metabolism. The sodium (Na^+) ion combines with bicarbonate ion produced from carbon dioxide of the body and thus retains bicarbonate to combat metabolic acidosis (bicarbonate deficiency). The normal plasma level of lactate ranges from 0.9 to 1.9 mEqK/liter.

Intravenous solutions containing potassium chloride are particularly intended to provide needed potassium cation (K^+). Potassium is the chief cation of body cells (160 mEq/liter of intracellular water). It is found in low concentration in plasma and extracellular fluids (3.5 to 5.0 mEq/liter in a healthy adult). Potassium plays an important role in electrolyte balance. Normally about 80 to 90% of the potassium intake is excreted in the urine; the remainder in the stools and to a small extent, in the perspiration. The kidney does not conserve potassium well so that during fasting or in patients on a potassium-free diet, potassium loss from the body continues resulting in potassium depletion. A deficiency of either potassium or chloride will lead to a deficit of the other.

Sodium chloride in water dissociates to provide sodium (Na^+) and chloride (Cl^-) ions. Sodium (Na^+) is the principal cation of the extracellular fluid and plays a large part in the therapy of fluid and electrolyte disturbances. Chloride (Cl^-) has an integral role in buffering action when oxygen and carbon dioxide exchange occurs in the red blood cells. The distribution and excretion of sodium (Na^+) and chloride (Cl^-) are largely under the control of the kidney which maintains a balance between intake and output.

Water is an essential constituent of all body tissues and accounts for approximately 70% of total body weight. Average normal adult daily requirement ranges from two to three liters (1.0 to 1.5 liters each for insensible water loss by perspiration and urine production).

Water balance is maintained by various regulatory mechanisms. Water distribution depends primarily on the concentration of electrolytes in the body compartments and sodium (Na+) plays a major role in maintaining physiologic equilibrium.

INDICATIONS AND USAGE

This solution is indicated in patients requiring parenteral administration of potassium chloride and the replacement of extracellular losses of fluids and electrolytes with minimal carbohydrate calories.

CONTRAINDICATIONS

Solutions containing potassium chloride are contraindicated in diseases where high potassium levels may be encountered.

Solutions containing lactate are NOT FOR USE IN THE TREATMENT OF LACTIC ACIDOSIS.

WARNINGS

Solutions containing calcium ions should not be administered simultaneously through the same administration set as blood because of the likelihood of coagulation.

Solutions which contain potassium ions should be used with great care, if at all, in patients with hyperkalemia, severe renal failure and in conditions in which potassium retention is present.

To avoid potassium intoxication, do not infuse these solutions rapidly. In patients with severe renal insufficiency or adrenal insufficiency, administration of potassium chloride may cause potassium intoxication.

Solutions containing sodium ions should be used with great care, if at all, in patients with congestive heart failure, severe renal insufficiency and in clinical states in which there exists edema with sodium retention.

In patients with diminished renal function, administration of solutions containing sodium or potassium ions may result in sodium or potassium retention.

Solutions containing lactate ions should be used with great care in patients with metabolic or respiratory alkalosis. The administration of lactate ions should be done with great care where there is an increased level or an impaired utilization of lactate ions, as in severe hepatic insufficiency.

The intravenous administration of this solution can cause fluid and/or solute overloading resulting in dilution of serum electrolyte concentrations, overhydration, congested states or pulmonary edema.

The risk of dilutional states is inversely proportional to the electrolyte concentration of administered parenteral solutions. The risk of solute overload causing congested states with peripheral and pulmonary edema is directly proportional to the electrolyte concentrations of such solutions.

PRECAUTIONS

Clinical evaluation and periodic laboratory determinations are necessary to monitor changes in fluid balance, electrolyte concentrations and acid-base balance during prolonged parenteral therapy or whenever the condition of the patient warrants such evaluation.

Solutions containing dextrose should be used with caution in patients with known subclinical or overt diabetes mellitus.

Caution must be exercised in the administration of parenteral fluids, especially those containing sodium ions, to patients receiving corticosteroids or corticotropin.

Potassium replacement therapy should be guided primarily by serial electrocardiograms. Plasma potassium levels are not necessarily indicative of tissue potassium levels.

High plasma concentrations of potassium may cause death through cardiac depression, arrhythmias or arrest.

Potassium-containing solutions should be used with caution in the presence of cardiac disease, particularly in digitalized patients or in the presence of renal disease.

Solutions containing lactate ions should be used with caution as excess administration may result in metabolic alkalosis.

Care should be exercised to insure that the needle (or catheter) is well within the lumen of the vein and that extravasation does not occur.

Do not administer unless solution is clear and container is undamaged. Discard unused portion.

PREGNANCY

Pregnancy. Animal reproduction studies have not been conducted with dextrose, potassium chloride or Lactated Ringer's Injection. It is also not known whether dextrose, potassium chloride or Lactated Ringer's Injection can cause fetal harm when administered to a pregnant woman or can affect reproduction capacity. Dextrose, potassium chloride or Lactated Ringer's Injection should be given to a pregnant woman only if clearly needed.

Pediatric Use:

The safety and effectiveness in the pediatric population are based on the similarity of the clinical conditions of the pediatric and adult populations. In neonates or very small infants the volume of fluid may affect fluid and electrolyte balance.

Frequent monitoring of serum glucose concentrations is required when dextrose is prescribed to pediatric patients, particularly neonates and low birth weight infants.

In very low birth weight infants, excessive or rapid administration of dextrose injection may result in increased serum osmolality and possible intracerebral hemorrhage.

ADVERSE REACTIONS

Reactions which may occur because of the solutions or technique of administration include febrile response, infection at the site of injection, venous thrombosis or phlebitis extending from the site of injection, extravasation and hypervolemia.

If an adverse reaction does occur, discontinue the infusion, evaluate the patient, institute appropriate therapeutic countermeasures and save the remainder of the fluid for examination if deemed necessary.

Nausea, vomiting, abdominal pain and diarrhea have been reported with potassium therapy. The signs and symptoms of potassium intoxication include paresthesias of the extremities, flaccid paralysis, listlessness, mental confusion, weakness and heaviness of the legs, hypotension, cardiac arrhythmias, heart block, electrocardiographic abnormalities such as disappearance of P waves, spreading and slurring of the QRS complex with development of a biphasic curve and cardiac arrest.

Potassium-containing solutions are intrinsically irritating to tissues. Therefore, extreme care should be taken to avoid perivascular infiltration. Local tissue necrosis and subsequent sloughing may result if extravasation occurs. Chemical phlebitis and venospasm have also been reported.

Should perivascular infiltration occur, I.V. administration at that site should be discontinued at once. Local infiltration of the affected area with procaine hydrochloride, 1%, to which hyaluronidase may be added, will often reduce venospasm and dilute the potassium remaining in the tissues locally. Local application of heat may also be helpful.

To report SUSPECTED ADVERSE REACTIONS, contact Fresenius Kabi USA, LLC at 1-800-551-7176 or FDA at 1-800-FDA-1088 or www.fda.gov/medwatch.

OVERDOSAGE

In the event of potassium overdosage, discontinue the infusion immediately and institute intensive corrective therapy to reduce serum potassium levels. See WARNINGS and PRECAUTIONS.

DOSAGE AND ADMINISTRATION

This solution should be administered only by intravenous infusion and as directed by the physician. The dose and rate of injection are dependent upon the age, weight and clinical condition of the patient. If the serum potassium level is greater than 2.5 mEq/liter, potassium should be given at a rate not to exceed 10 mEq/hour in a concentration less than 30 mEq/liter. Somewhat faster rates and greater concentrations (usually up to 40 mEq/liter) of potassium may be indicated in patients with more severe potassium deficiency. The total 24-hour dose should not generally exceed 200 mEq of potassium.

As reported in the literature, the dosage and constant infusion rate of intravenous dextrose must be selected with caution in pediatric patients, particularly neonates and low birth weight infants, because of the increased risk of hyperglycemia/hypoglycemia.

Drug Interactions

Additives may be incompatible. Consult with pharmacist, if available. When introducing additives, use aseptic technique, mix thoroughly and do not store.

The presence of calcium limits their compatibility with certain drugs that form precipitates of calcium salts, and also prohibits their simultaneous infusion through the same administration set as blood because of the likelihood of coagulation.

Parenteral drug products should be inspected visually for particulate matter and discoloration prior to administration, whenever solution and container permit. See PRECAUTIONS.

HOW SUPPLIED

Potassium Chloride (20 mEq Added) in Lactated Ringer's and 5% Dextrose Injection, USP is supplied in single-dose freeflex® plastic containers as follows:

Product Code | Unit of Use | Unit of Sale
360236 | NDC 65219-246-00 One 1000 mL freeflex® bag | NDC 65219-246-10 Package of 10 freeflex® bags

Store at 20 to 25°C (68 to 77°F). [See USP Controlled Room Temperature.] Avoid excessive heat. Protect from freezing.

The container closure is not made with natural rubber latex. Non-PVC, Non-DEHP, Sterile.

INSTRUCTIONS FOR USE

Check flexible container solution composition, lot number, and expiry date.

Do not remove solution container from its overwrap until immediately before use. Use sterile equipment and aseptic technique.

Flexible Plastic Container (freeflex® bag)

To Open

1. Turn solution container over so that the text is face down. Using the pre-cut corner tabs, peel open the overwrap and remove solution container.
2. Check the solution container for leaks by squeezing firmly. If leaks are found, or if the seal is not intact, discard the solution.
3. Do not use if the solution is cloudy or a precipitate is present.

To Add Medication

1. Identify WHITE Additive Port with arrow pointing toward container.
2. Immediately before injecting additives, break off WHITE Additive Port Cap with the arrow pointing toward container.
3. Hold base of WHITE Additive Port horizontally.
4. Insert needle horizontally through the center of WHITE Additive Port's septum and inject additives.
5. Mix container contents thoroughly.

Preparation for Administration

1. Immediately before inserting the infusion set, break off BLUE Infusion Port Cap with the arrow pointing away from container.
2. Use a non-vented infusion set or close the air-inlet on a vented set.
3. Close the roller clamp of the infusion set.
4. Hold the base of BLUE Infusion Port.
5. Insert spike through BLUE Infusion Port by rotating wrist slightly until the spike is inserted. NOTE: See full directions accompanying administration set.

WARNING: Do not use flexible container in series connections.

Manufactured for:

Lake Zurich, Illinois 60047

Made in Norway

451662

www.fresenius-kabi.com/us

Issued: September 2022

PACKAGE LABEL - PRINCIPAL DISPLAY –Potassium Chloride in Lactated Ringer's and 5% Dextrose Bag Label

20mEq POTASSIUM ADDED
1000 mL NDC 65219-246-00 freeflex®

20 mEq POTASSIUM CHLORIDE in Lactated Ringer's and 5% Dextrose Injection, USP

Rx only

PACKAGE LABEL - PRINCIPAL DISPLAY –Potassium Chloride in Lactated Ringer's and 5% Dextrose Case Label

NDC 65219-246-10 360236
20 mEq Potassium Chloride in Lactated Ringer's and 5% Dextrose Injection, USP

1000 mL x 10

Store at 20° to 25°C (68° to 77°F)
[see USP Controlled Room Temperature].

Avoid excessive heat. Protect from freezing.